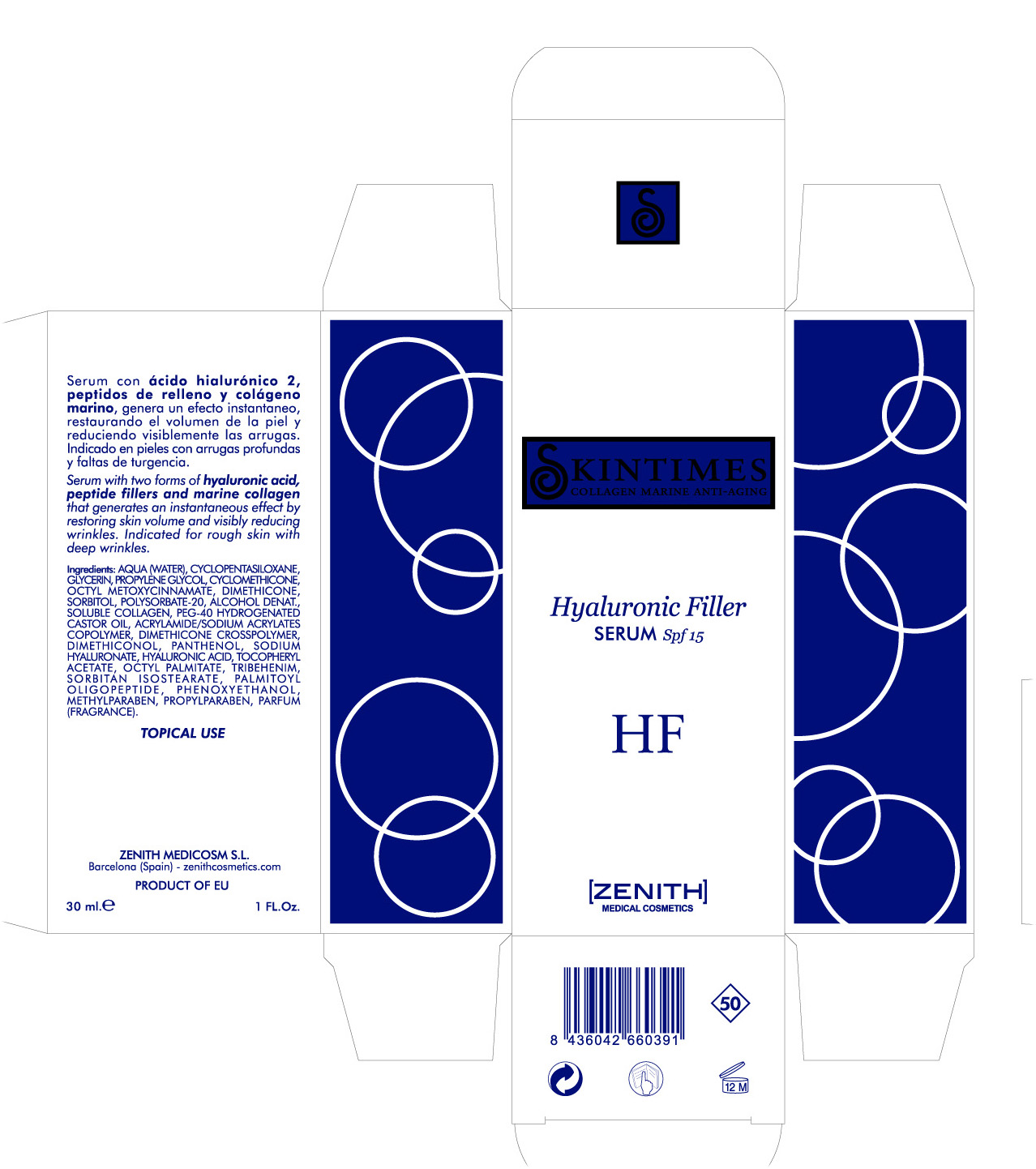 DRUG LABEL: Hyaluronic Filler
NDC: 42248-125 | Form: CREAM
Manufacturer: Zenith Medicosm SL
Category: otc | Type: HUMAN OTC DRUG LABEL
Date: 20120220

ACTIVE INGREDIENTS: OCTINOXATE 2.25 mL/30 mL
INACTIVE INGREDIENTS: CYCLOMETHICONE 5; PROPYLPARABEN; ALPHA-TOCOPHEROL ACETATE; PROPYLENE GLYCOL; CYCLOMETHICONE; DIMETHICONE; WATER; SORBITOL; POLYSORBATE 20; ALCOHOL; POLYOXYL 40 HYDROGENATED CASTOR OIL; GLYCERIN; TROLAMINE; ISOBUTYLPARABEN; ACRYLAMIDE; SODIUM ACRYLATE; DIMETHICONOL (250000 MW); PANTHENOL; METHYLPARABEN; COLLAGEN, SOLUBLE, FISH SKIN; PHENOXYETHANOL; HYALURONATE SODIUM; HYALURONIC ACID; ETHYLHEXYL PALMITATE; TRIBEHENIN; SORBITAN ISOSTEARATE; PALMITOYL OLIGOPEPTIDE

Drug Facts

Active Ingredient

Octinoxate 7.5%

Description

Serum with two forms of hyaluronic cid, peptide fillers and marine collagen that generates an instantaneous effect by restoring skin volume and visibly reducing wrinkles. Indicated for rough skin with deep wrinkles.

30 ml. 1 FL. Oz

Warning

TOPICAL USE